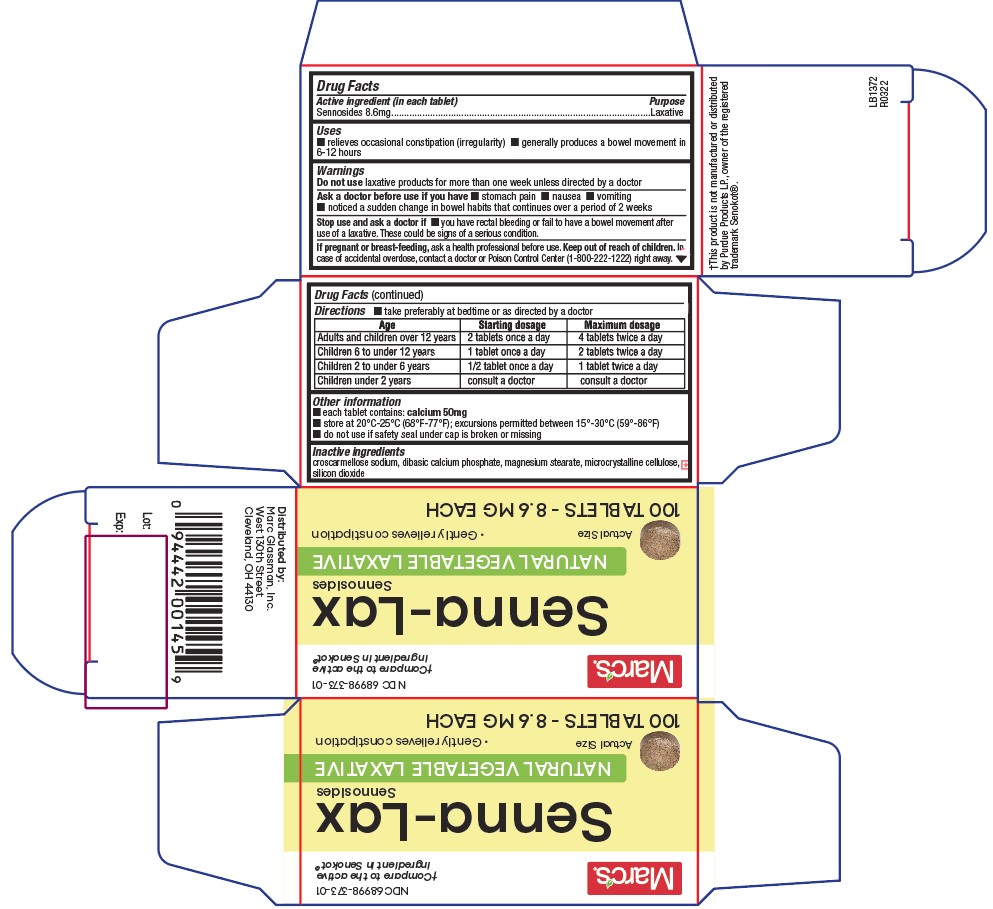 DRUG LABEL: Senna-Lax
NDC: 68998-373 | Form: TABLET
Manufacturer: Marc Glassman, Inc.
Category: otc | Type: HUMAN OTC DRUG LABEL
Date: 20161227

ACTIVE INGREDIENTS: SENNOSIDES 8.6 mg/1 1
INACTIVE INGREDIENTS: CROSCARMELLOSE SODIUM; MAGNESIUM STEARATE; MICROCRYSTALLINE CELLULOSE; SILICON DIOXIDE

371 - Senna-Lax

Active ingredient

Sennosides 8.6 mg

Purpose

Laxative

Uses

- for relief of occasional constipation (irregularity)
- this product produces a bowel movement in 6 to 12 hours

Warnings

Do not use

laxative products for more than one week unless directed by a doctor

Ask a doctor before use if you have

- stomach pain
- nausea
- vomiting
- noticed a sudden change in bowel habits that continues over a period of 2 weeks

Stop use and ask a doctor if

- rectal bleeding or failure to have a bowel movement occur after use of a laxative. These could be signs of a serious condition.

If pregnant or breast-feeding,

ask a health professional before use.

Keep out of reach of children

In case of accidental overdose, contact a doctor or Poison Control Center (1-800-222-1222) right away.

Directions

- take preferably at bedtime or as directed by a doctor

Age | Starting dosage | Maximum dosage
Adults and children over 12 years | 2 tablets once a day | 4 tablets twice a day
Children 6 to under 12 years | 1 tablet once a day | 2 tablets twice a day
Children 2 to under 6 years | 1/2 tablet once a day | 1 tablet twice a day
Children under 2 years | consult a doctor | consult a doctor

Other information

■ store at 20°C-25°C (68°F-77°F)

■ do not use if safety seal under cap is torn or missing

■ Calcium content: 50 mg per tablet

Inactive ingredients

croscarmellose sodium, dibasic calcium phosphate, magnesium stearate, microcrystalline cellulose, silicon dioxide

Principal Display Panel

Senna Lax

68998-373-01

†Compare to the Active Ingredient in Senokot®

Marc's (logo)

Senna-Lax

NATURAL VEGETABLE LAXATIVE

Gently Relieves Constipation

100 Tablets